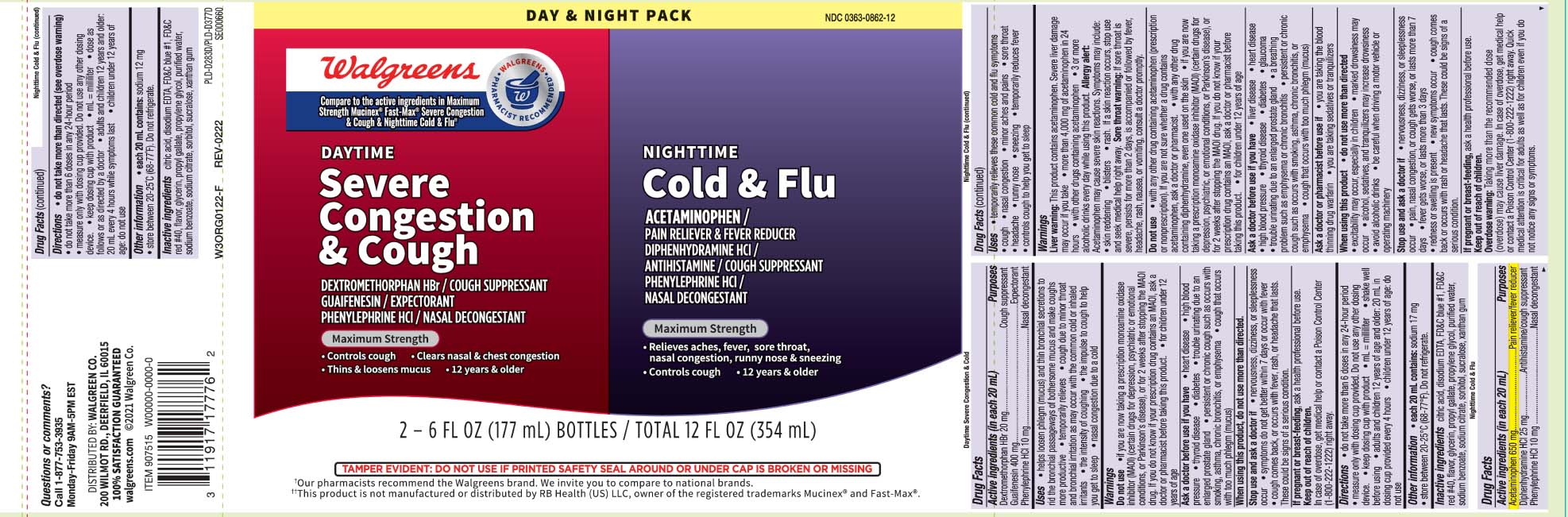 DRUG LABEL: Daytime Mucus Relief Severe Congestion and Cough and Nighttime Cold and Flu
NDC: 0363-0862 | Form: KIT | Route: ORAL
Manufacturer: Walgreens
Category: otc | Type: HUMAN OTC DRUG LABEL
Date: 20240716

ACTIVE INGREDIENTS: DEXTROMETHORPHAN HYDROBROMIDE 20 mg/20 mL; GUAIFENESIN 400 mg/20 mL; PHENYLEPHRINE HYDROCHLORIDE 10 mg/20 mL; ACETAMINOPHEN 650 mg/20 mL; DIPHENHYDRAMINE HYDROCHLORIDE 25 mg/20 mL; PHENYLEPHRINE HYDROCHLORIDE 10 mg/20 mL
INACTIVE INGREDIENTS: FD&C BLUE NO. 1; PROPYLENE GLYCOL; WATER; FD&C RED NO. 40; ANHYDROUS CITRIC ACID; EDETATE CALCIUM DISODIUM; SODIUM BENZOATE; TRISODIUM CITRATE DIHYDRATE; GLYCERIN; PROPYL GALLATE; SORBITOL; SUCRALOSE; XANTHAN GUM; GLYCERIN; PROPYLENE GLYCOL; WATER; SORBITOL; ANHYDROUS CITRIC ACID; FD&C BLUE NO. 1; FD&C RED NO. 40; SODIUM BENZOATE; SODIUM CITRATE; SUCRALOSE; PROPYL GALLATE; XANTHAN GUM; EDETATE CALCIUM DISODIUM

DRUG FACTS

Active ingredients for Nighttime (in each 20 mL)

Acetaminophen 650 mg

Diphenhydramine HCI 25 mg

Phenylephrine HCI 10 mg

Active ingredients for Daytime (in each 20 mL)

Dextromethorphan HBr 20 mg

Guaifeenesin 400 mg

Phenylephrine HCl 10 mg

Purpose for Nighttime

Pain reliever/fever reducer

Antihistamine/cough suppressant

Nasal decongestant

Purpose for Daytime

Cough suppressant

Expectorant

Nasal decongestant

Uses

Nighttime

- temporarily relieves these common cold and flu symptoms
- cough
- nasal congestion
- minor aches and pains
- sore throat
- headache
- runny nose
- sneezing
- temporarily reduces fever
- controls cough to help you get to sleep

Daytime

- helps loosen phlegm (mucus) and thin bronchial secretions to rid the bronchial passageway of bothersome mucus and make coughs more productive
- temporarily relieves
  - cough due to minor throat and bronchial irritation as may occur with the common cold or inhaled irritants
  - the intensity of coughing
  - the impulse to cough to help you get to sleep
  - nasal congestion due to a cold

Warnings

NIGHTTIME

Liver warning: This product contain acetaminophen. Severe liver damage may occur if you take

- more than 4,000 mg of acetaminophen in 24 hours
- with other drugs containing acetaminophen
- 3 or more alcoholic drinks every day while using this product.

Allergy alert: Acetaminophen may cause severe skin reactions. Symptoms may include:

- skin reddening
- blisters
- rash.

If a skin reaction occurs, stop use and seek medical help right away.

Sore throat warning: If sore throat is severe, persists for more than 2 days, is accompanied or followed by fever, headache, rash, nausea, or vomiting, consult a doctor promptly.

Do not use

Nighttime

- with any drug containing acetaminophen (prescription or nonprescription) . If you are not sure whether a drug contains acetaminophen, ask a doctor or pharmacist.
- with any other drug containing diphenhydramine, even one used on the skin
- if you are now taking a prescription monoamine oxidase inhibitor (MAOI) (certain drugs for depression, psychiatric or emotional conditions, or Parkinson’s disease), or for 2 weeks after stopping the MAOI drug. If you do not know if your prescription drug contains an MAOI, ask a doctor or pharmacist before taking this product
- for children under 12 years of age

Daytime

- if you are now taking a prescription monoamine oxidase inhibitor (MAOI)(certain drugs for depression,psychiatic or emotional conditions, or Parkinson's disease), or for 2 weeks after stopping the MAOI drug. If you do not know if your prescription drug contains an MAOI, ask a doctor or pharmacist before taking this product.
- for children under 12 years of age

Ask a doctor before use if you have

Nighttime

- liver disease
- heart disease
- high blood pressure
- thyroid disease
- diabetes
- glaucoma
- trouble urinating due to an enlarged prostate gland
- a breathing problem such as emphysema or chronic bronchitis
- persistent or chronic cough such as occurs with smoking, asthma, chronic bronchitis, or emphysema
- cough that occurs with too much phlegm (mucus)

Daytime

- heart disease
- high blood pressure
- thyroid disease
- diabetes
- trouble urinating due to an enlarged gland
- persistent or chronic cough such as occurs with smoking, asthma, chronic bronchitis, or emphtsema
- cough that occurs with too much phlegm (mucus)

Ask a doctor or pharmacist before use if you are

Nighttime

- taking the blood thinning drug warfarin
- taking sedative or tranquilizers

When using these products

Nighttime

- do not use more than directed
- excitability may occur, especially in children
- marked drowsiness may occur
- alcohol, sedatives and tranquilizers may increase drowsiness
- avoid alcoholic drinks
- be careful when driving a motor vehicile or operating machinery

Daytime

- do not use more than directed

Stop use and ask a doctor if

Nighttime

- nervousness, dizziness, or sleeplessness occur
- pain, nasal congestion, or cough gets worse, or lasts more than 7 days
- fever gets worse, or last more than 3 days
- redness or swelling is present
- new symptoms occur
- cough comes back or occurs with rash or headache that lasts. These could be a signs of a serious condition

Daytime

- nervousness, dizziness or sleeplessness occur
- symptoms do not get better within 7 days or occur with fever
- cough comes back, or occur with fever, rash, or headache that lasts. These could be signs of a serious condition.

If pregnant or breast-feeding,

Nighttime

ask a health professional before use.

Daytime

ask a health professional before use

Keep out of reach of children.

Nighttime

Overdose warning: Taking more than the recommended dose (overdose) may cause liver damage. In case of overdose, get medical help or contact a Poison Control Center (1-800-222-1222) right away. Quick medical attention is critical for adults as well as for children even if you do not notice any signs or symptoms.

Daytime

In case of overdose, get medical help or contact a Poison Control Center (1-800-222-1222) right away.

Directions

Nighttime

- do not take more than directed (see overdose warning)
- do not take more than 6 doses in any 24-hour period
- measure only with dosing cup provided. Do not use any other dosing device
- keep dosing cup with product
- mL = mililiter
- dose as follows or as directed by a doctor
- adults and children 12 years and older: 20 mL every 4 hours while symptoms last
- children under 12 years of age: do not use

Daytime

- do not take more than 6 doses in any 24-hours period
- measure only with dosing cup provided. Do not use any other dosing device.
- keep dosing cup with product
- mL = mililiter
- shake well before using
- adults and children 12 years of age and older: 20 mL in dosing cup provided every 4 hours
- children under 12 years of age: do not use

Other information

Nighttime

- each 20 mL contains: sodium 12 mg
- store between 20-25ºC (68-77ºF). Do not refrigerate.

Daytime

- each 20 mL contains: 17 mg
- store between 20-25ºC (68-77ºF). Do not refrigerate.

Inactive ingredients

Nighttime

citric acid, disodium EDTA, FD&C Blue #1, FD&C red #40, Flavor, glycerin, propyl gallate, propylene glycol, purified water, sodium benzoate, sodium citrate, sorbitol, sucralose, xanthan gum

Daytime

citric acid, disodium EDTA, FD&C blue #1, FD&C red #40, flavor, glycerin, propyl gallate, propylene glycol, purified water, sodium benzoate, sodium citrate, sorbitol, sucralose, xanthan gum

Questions or comments?

Nighttime

Call 1-877-753-3935 Monday- Friday 9AM- 5PM EST

Daytime

Call 1-877-753-3935 Monday-Friday 9AM-5PM EST

Principal Display Panel

Compare to Maximum Strength Mucinex® Fast-Max® Severe Congestion & Cough & Night Time Cold & Flu active ingredient††

NIGHTTIME

Cold & Flu

ACETAMINOPHEN /

PAIN RELIEVER & FEVER REDUCER

DIPHENHYDRAMINE HCI /

ANTIHISTAMINE / COUGH SUPPRESSANT

PHENYLEPHRINE HCI /

NASAL DECONGESTANT

MAXIMUM STRENGTH

- Relieves aches, fever, sore throat, nasal congestion, runny nose, & sneezing
- Controls cough
- For ages 12 & over

DAYTIME

Severe Congestion & Cough

DEXTROMETHORPHAN HBr /

COUGH SUPPRESSANT

GUAIFENESIN / EXPECTORANT

PHENYLEPHRINE HCI / NASAL DECONGESTANT

MAXIMUM STRENGTH

- Controls Cough
- Clears nasal & chest congestion
- Thins & loosens mucus
- For ages 12 & over

TAMPER EVIDENT: DO NOT USE IF PRINTED SAFETY SEAL AROUND OR UNDER CAP IS BROKEN OR MISSING.

††This product is not manufactured or distributed by Reckitt Benckiser, distributor of Maximum Strength Mucinex® FAST-MAX® Severe Congestion & Cough & Nighttime Cold & Flu.

DISTRIBUTED BY: WALGREEN CO.

200 WILMOT RD., DEERFIELD, IL 60015

walgreens.com

Product Label

WALGREENS Daytime Severe Congestion & Cough Nighttime Cold & Flu